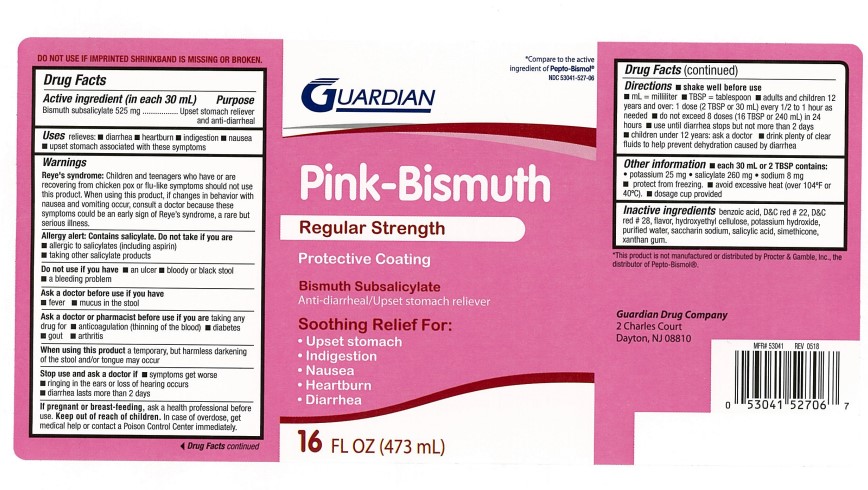 DRUG LABEL: Pink-Bismuth
                
NDC: 53041-527 | Form: LIQUID
Manufacturer: Guardian Drug Company
Category: otc | Type: HUMAN OTC DRUG LABEL
Date: 20251203

ACTIVE INGREDIENTS: BISMUTH SUBSALICYLATE 262 mg/15 mL
INACTIVE INGREDIENTS: BENZOIC ACID; D&C RED NO. 22; D&C RED NO. 28; HYDROXYETHYL CELLULOSE (2000 CPS AT 1%); POTASSIUM HYDROXIDE; WATER; SACCHARIN SODIUM; SALICYLIC ACID; DIMETHICONE; XANTHAN GUM

Pink-Bismuth Regular Strength

Active ingredient (in each 15 mL tbsp)

Bismuth subsalicylate 262 mg

Purpose

Upset stomach reliever and anti-diarrheal

Uses

relieves:

- diarrhea
- heartburn
- indigestion
- nausea
- upset stomach associated with these symptoms

Warnings

Reye's syndrome: Children and teenagers who have or are recovering from children pox or flu-like symptoms should not use this product. when using this product, if changes in behavior with nausea and vomiting occur, consult a doctor because these symptoms could be an early sign of Reye's syndrome, a rare but serious illness.

Allergy alert: Contains salicylate. Do not take if you are

- allergic to salicylates (including aspirin)
- taking other salicylate products

Do not use if you have

- bloody or black stool
- an ulcer
- a bleeding problem

Ask a doctor before use if you have

- fever
- mucus in the stool

Ask a doctor or pharmacist before use if you are taking any drug for

- anticoagulation (thinning of the blood)
- diabetes
- gout
- arthritis

When using this product

a temporary, but harmless darkening of the stool and/or tongue may occur

Stop use and ask a doctor if

- symptoms get worse
- ringing in the ears or loss of hearing occurs
- diarrhea lasts more than 2 days

If pregnant or breast feeding, ask a health professional before use. Keep out of reach of children.

In case of overdose, get medical help or contact a Poison control center immediately.

Directions

- shake well before use
- for accurate dosing, use dose cup
- adults and children 12 years and over: 1 dose (2 tbsp or 30 mL) every 1/2 to 1 hour as needed
- do not exceed 8 doses (16 tbsp or 240 mL) in 24 hours
- use until diarrhea stops but not more than 2 days
- children under 12 years: ask a doctor
- drink plenty of clear fluids to help prevent dehydration caused by diarrhea

Other information

- each Tbsp contains: sodium 5 mg, salicylate 130 mg, potassium 15 mg
- protect from freezing
- avoid excessive heat (over 104oF or 40oC)
- TAMPER EVIDENT: Do not use if imprinted shrinkband is missing or broken.

Inactive ingredients

benzoic acid, D and C red 22, D and C red 28, flavor, hydroxy ethyl cellulose, potassium hydroxide, purified water, saccharin sodium, salicylic acid, simethicone, xanthan gum.

Principal Display Panel

compare to the active ingredient in pepto-bismol®

Pink-Bismuth

Regular Strength

Protective coating

Bismuth subsalicylate

Anti-diarrheal/Upset stomach reliever

Soothing Relief For:

upset stomach

Indigestion

Nausea

Heartburn

Diarrhea

16 FL OZ (473 mL)